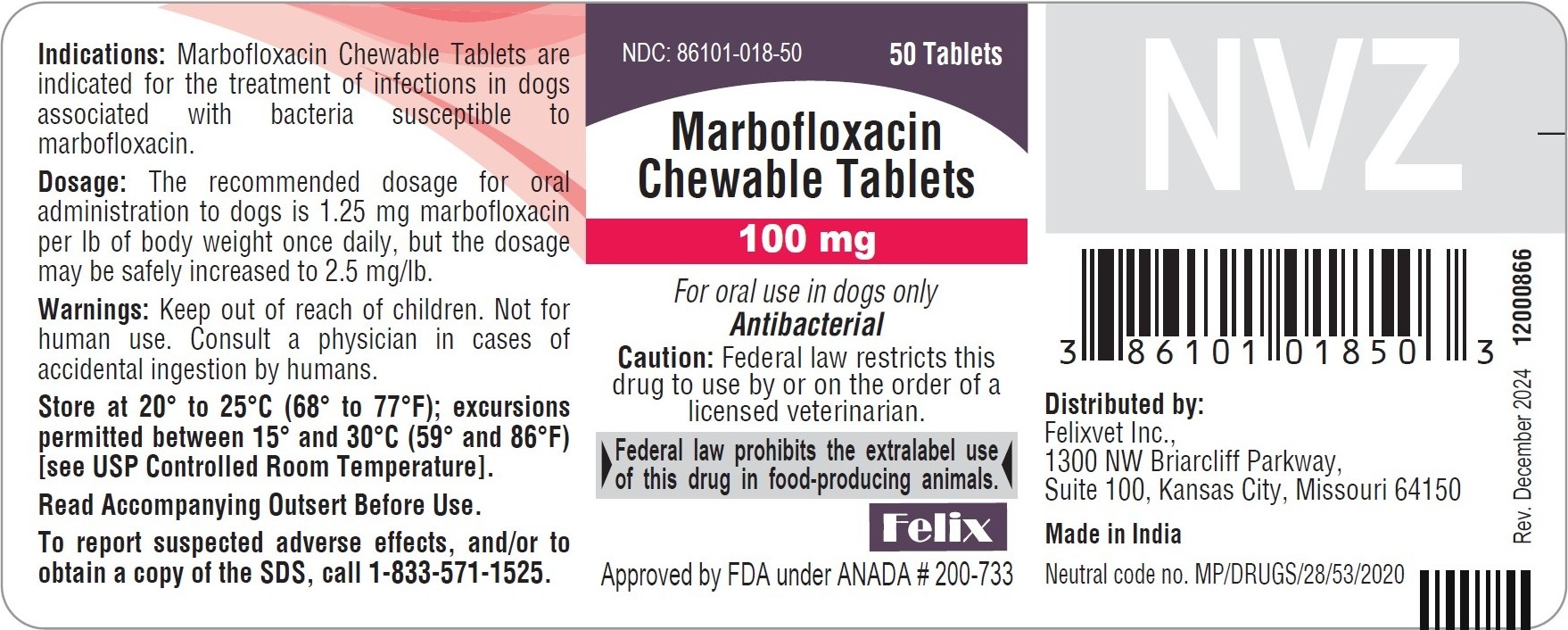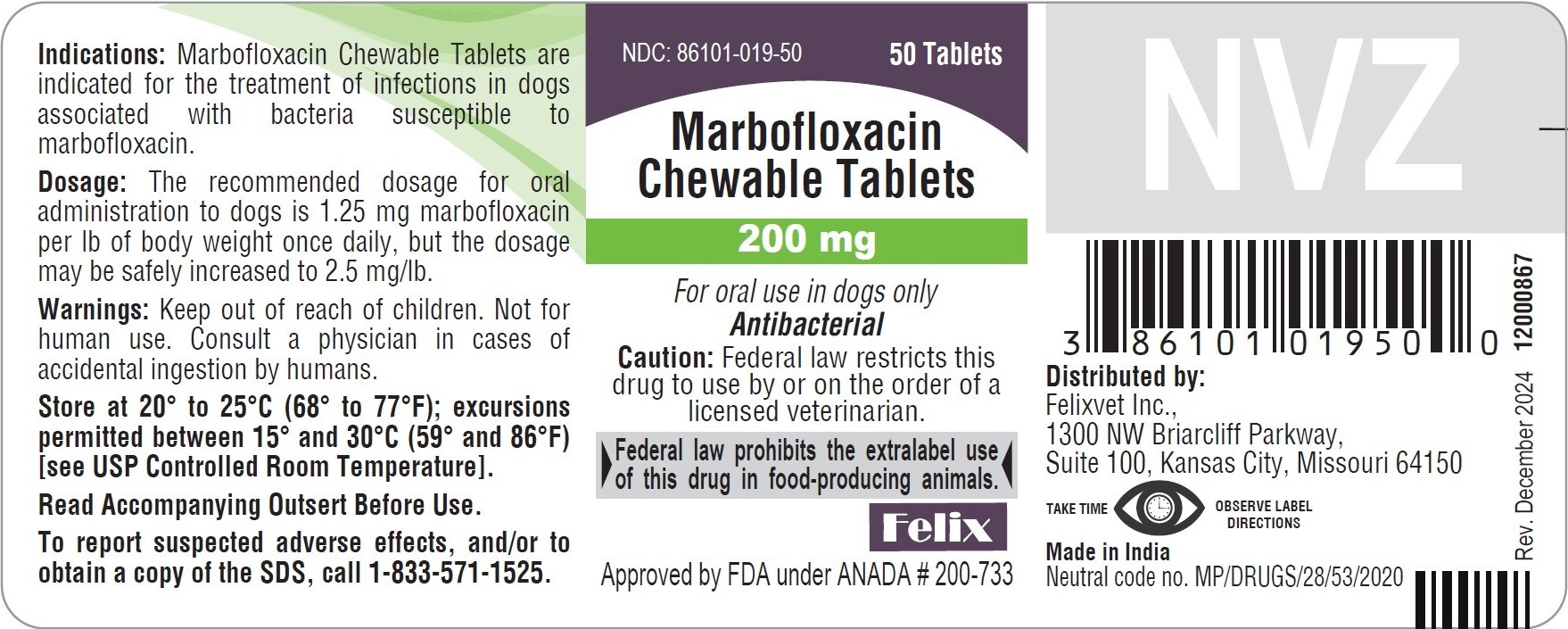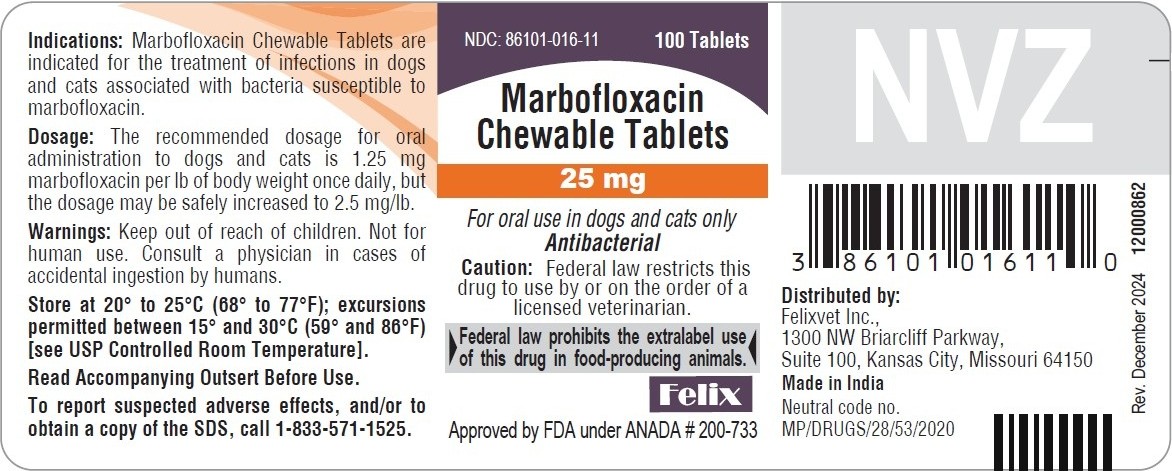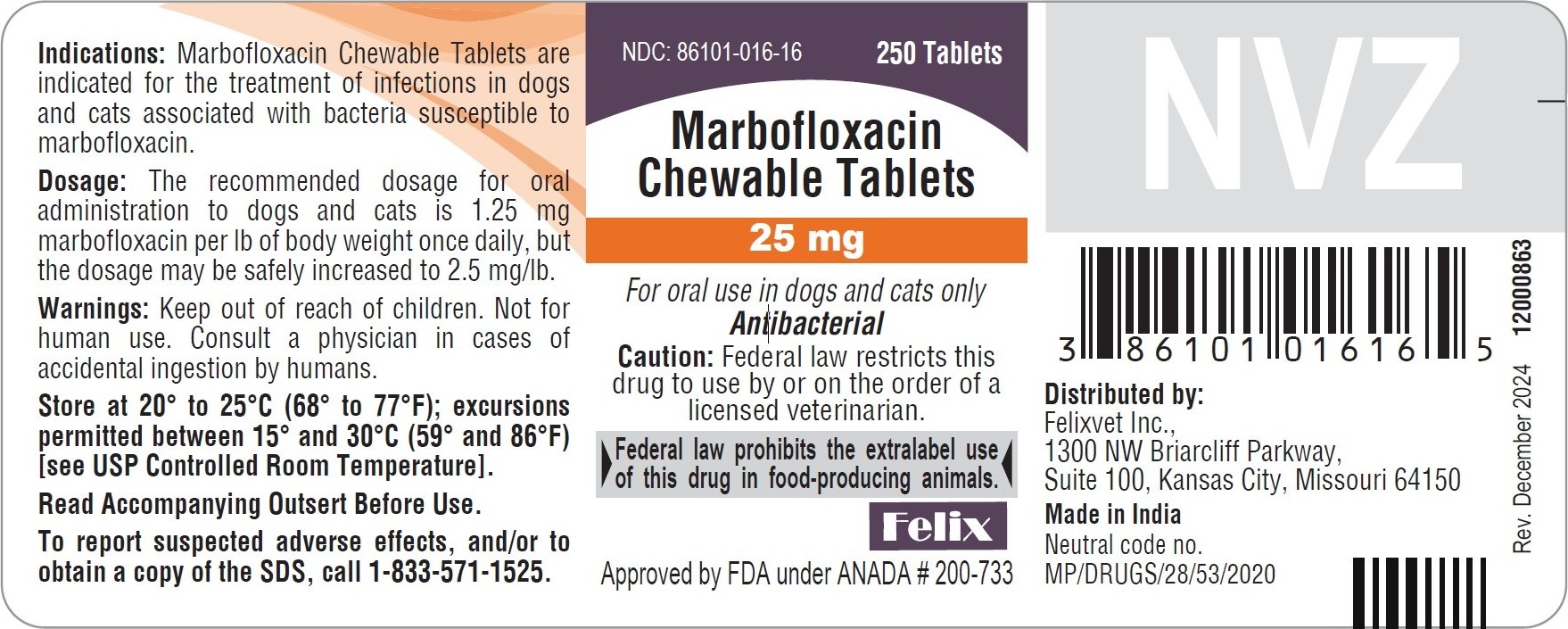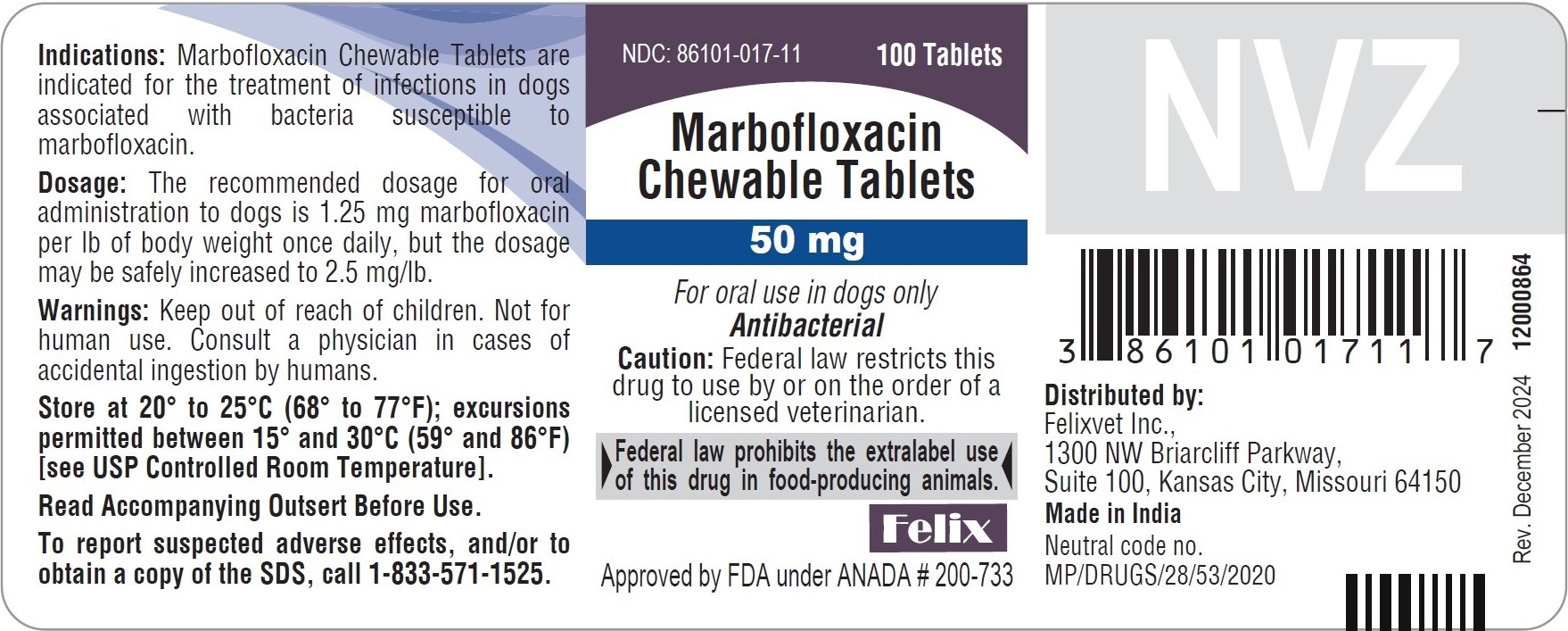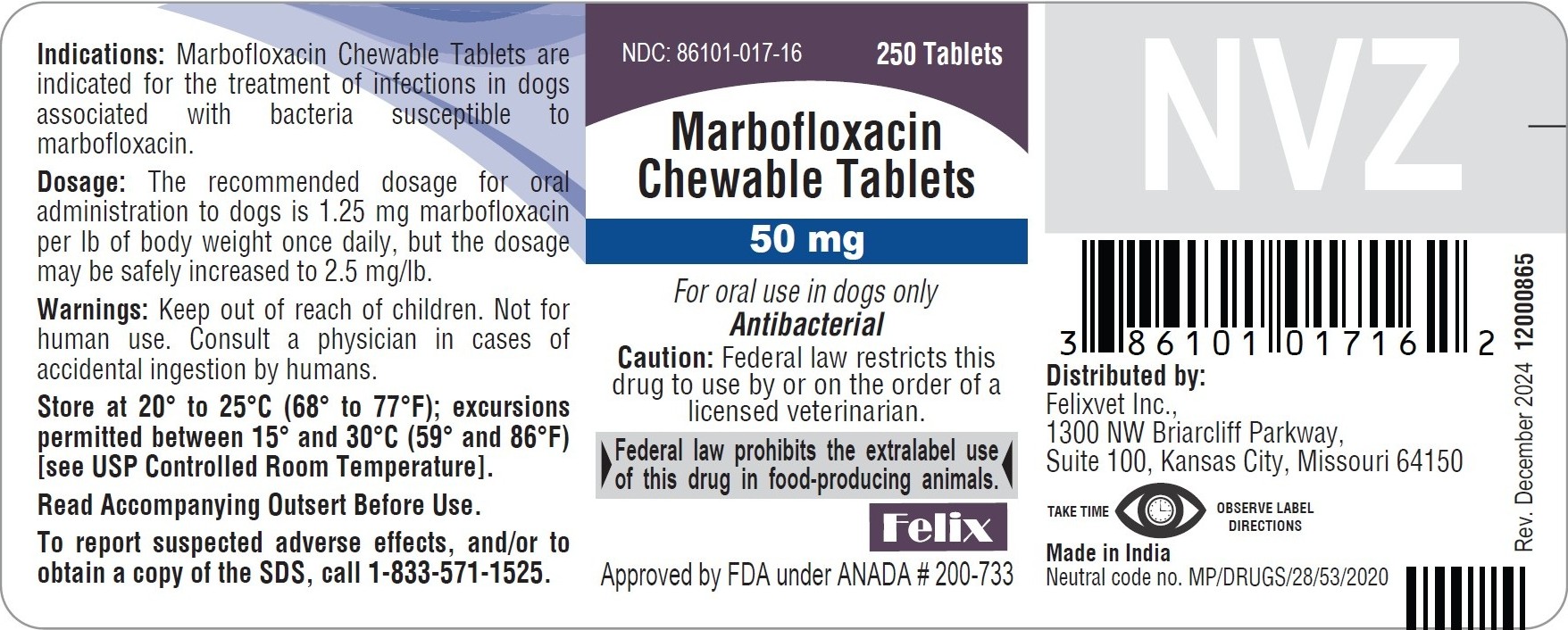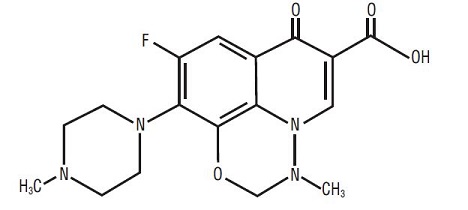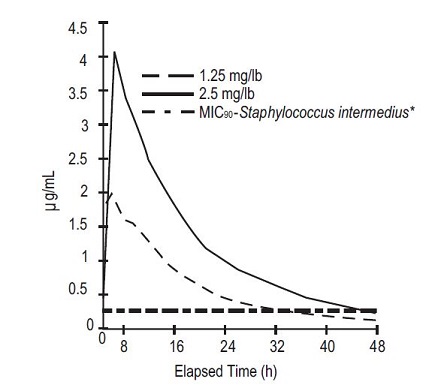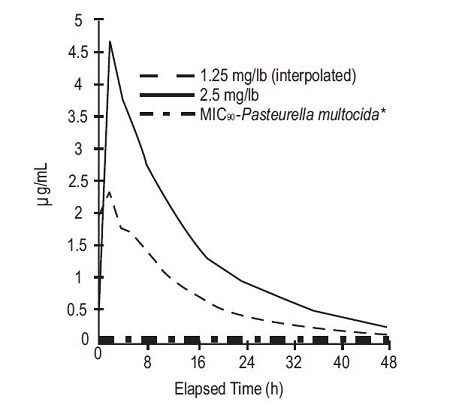 DRUG LABEL: Marbofloxacin
NDC: 86101-016 | Form: TABLET, CHEWABLE
Manufacturer: FELIX PHARMACEUTICALS PRIVATE LIMITED
Category: animal | Type: Prescription Animal Drug Label
Date: 20260218

ACTIVE INGREDIENTS: MARBOFLOXACIN 25 mg/1 1

Marbofloxacin
Chewable Tablets
For oral use in dogs and cats only

CAUTION: Federal law restricts this drug to use by or on the order of a licensed veterinarian.

Federal law prohibits the extralabel use of this drug in food-producing animals.

DESCRIPTION:

Marbofloxacin is a synthetic broad-spectrum antibacterial agent from the fluoroquinolone class of chemotherapeutic agents. Marbofloxacin is the non-proprietary designation for 9-fluoro-2,3-dihydro-3-methyl-10-(4-methyl-1-piperazinyl)-7-oxo-7H-pyrido[3,2,1-ij][4,1,2] benzoxadiazine-6-carboxylic acid. The empirical formula is C17H19FN4O4 and the molecular weight is 362.36. The compound is soluble in water; however, solubility decreases in alkaline conditions. The N-octanol/water partition coefficient (Kow) is 0.835 measured at pH 7 and 25°C.

Figure 1: Chemical structure of marbofloxacin

CLINICAL PHARMACOLOGY:

Marbofloxacin is rapidly and almost completely absorbed from the gastrointestinal tract following oral administration to fasted animals. Divalent cations are generally known to diminish the absorption of fluoroquinolones. The effects of concomitant feeding on the absorption of marbofloxacin have not been determined. (See Drug Interactions.) In the dog, approximately 40% of an oral dose of marbofloxacin is excreted unchanged in the urine^1. Excretion in the feces, also as unchanged drug, is the other major route of elimination in dogs. Ten to 15% of marbofloxacin is metabolized by the liver in dogs.

In vitro plasma protein binding of marbofloxacin in dogs was 9.1% and in cats was 7.3%. In the cat, approximately 70% of an oral dose is excreted in the urine as marbofloxacin and metabolites with approximately 85% of the excreted material as unchanged drug. Pharmacokinetic parameters related to intravenous dosing were estimated in a study of 6 healthy adult beagle dogs, and are summarized in Table 1. The absolute bioavailability following dosing of oral tablets to the same animals was 94%.

Marbofloxacin plasma concentrations were determined over time in healthy adult beagle dogs (6 dogs per dosage group) following single oral doses of 1.25 mg/lb or 2.5 mg/lb. Absorption of orally administered marbofloxacin increases proportionally over the dose range of 1.25 to 2.5 mg/lb. Marbofloxacin plasma concentrations were determined over time in 7 healthy adult male cats following a single oral dose of 2.5 mg/lb. Plasma pharmacokinetic parameters following oral dosing of dogs and cats are summarized in Figures 2 and 3 and in Table 2. Based on the terminal elimination half-life and the dosing interval, steady-state levels are reached after the third dose and are expected to be approximately 25% greater in dogs and 35% greater in cats than those achieved after a single dose. Marbofloxacin is widely distributed in canine tissues. Tissue concentrations of marbofloxacin were determined in healthy male beagle dogs (4 dogs per time period) at 2, 18 and 24 hours after a single oral dose (1.25 or 2.5 mg/lb) and are summarized in Tables 3a and 3b.

Table 1: Mean pharmacokinetic parameters following intravenous administration of marbofloxacin to 6 adult beagle dogs at a dosage of 2.5 mg/lb.

Parameter | Estimate ± SD* n=6
Total body clearance, (mL/h•kg) | 94 ± 8
Volume of distribution at steady state, Vss, (L/kg) | 1.19 ± 0.08
AUC0-inf (μg•h/mL) | 59 ± 5
Terminal plasma elimination half-life, t1/2(h) | 9.5 ± 0.7

*SD = standard deviation

Table 2: Mean pharmacokinetic parameters following oral administration of marbofloxacin tablets to adult beagle dogs at a nominal dosage of 1.25 mg/lb or 2.5 mg/lb and to cats at 2.5 mg/lb.†

Parameter | Dog Estimate ± SD* (1.25 mg/lb) n=6 | Dog Estimate ± SD* (2.5 mg/lb) n=6 | Cat Estimate ± SD* (2.5 mg/lb) n=7
Time of maximum concentration, Tmax(h) | 1.5 ± 0.3 | 1.8 ± 0.3 | 1.2 ± 0.6
Maximum concentration, Cmax, (μg/mL) | 2.0 ± 0.2 | 4.2 ± 0.5 | 4.8 ± 0.7
AUC0-inf (μg•h/mL) | 31.2 ± 1.6 | 64 ± 8 | 70 ± 6
Terminal plasma elimination half-life, t1/2(h) | 10.7 ± 1.6 | 10.9 ± 0.6 | 12.7 ± 1.1

† mean actual dosages administered to dogs were 1.22 mg/lb and 2.56 mg/lb, respectively, and the mean actual dosage administered to cats was 2.82 mg/lb.

* SD = standard deviation

Figure 2: Mean plasma concentrations (μg/mL) following single oral administration of marbofloxacin to adult beagle dogs at dosages of 1.25 mg/lb or 2.5 mg/lb.

* See Table 4 in Microbiology section for MIC data.

Figure 3: Mean plasma concentrations (µg/mL) following single oral administration of marbofloxacin to adult cats at a dosage of 2.5 mg/lb.

* See Table 5 in Microbiology section for MIC data.

Table 3a: Tissue distribution following a single oral administration of marbofloxacin tablets to adult beagle dogs at a dosage of 1.25 mg/lb*.

Tissue | Marbofloxacin 2 hours (n=4) | Concentrations 18 hours (n=4) | (μg/g ± SD) 24 hours (n=4)
bladder | 4.8 ± 1.1 | 2.6 ± 1.5 | 1.11 ± 0.19
bone marrow | 3.1 ± 0.5 | 1.5 ± 1.5 | 0.7 ± 0.2
feces | 15 ± 9 | 48 ± 40 | 26 ± 11
jejunum | 3.6 ± 0.5 | 1.3 ± 1.0 | 0.7 ± 0.3
kidney | 7.1 ±1.7 | 1.4 ± 0.5 | 0.9 ± 0.3
lung | 3.0 ± 0.5 | 0.8 ± 0.2 | 0.57 ± 0.19
lymph node | 5.5 ± 1.1 | 1.3 ± 0.3 | 1.0 ± 0.3
muscle | 4.1 ± 0.3 | 1.0 ± 0.3 | 0.7 ± 0.2
prostate | 5.6 ± 1.4 | 1.8 ± 0.6 | 1.1 ± 0.4
skin | 1.9 ± 0.6 | 0.41 ± 0.13 | 0.32 ± 0.08

*SD = standard deviation

Table 3b: Tissue distribution following a single oral administration of marbofloxacin tablets to adult beagle dogs at a dosage of 2.5 mg/lb.

Tissue | Marbofloxacin 2 hours (n=4) | Concentration 18 hours (n=4) | (μg/g ± SD*) 24 hours (n=4)
bladder | 12 ± 4 | 6 ± 7 | 1.8 ± 0.4
bone marrow | 4.6 ± 1.5 | 1.28 ± 0.13 | 0.9 ± 0.3
feces | 18 ± 3 | 52 ± 17 | 47 ± 28
jejunum | 7.8 ± 1.1 | 2.0 ± 0.3 | 1.1 ± 0.3
kidney | 12.7 ±1.7 | 2.7 ± 0.3 | 1.6 ± 0.2
lung | 5.48 ± 0.17 | 1.45 ± 0.19 | 1.0 ± 0.2
lymph node | 8.3 ± 0.7 | 2.3 ± 0.5 | 2.03 ± 0.06
muscle | 7.5 ± 0.5 | 1.8 ± 0.3 | 1.20 ± 0.12
prostate | 11 ± 3 | 2.7 ± 1.0 | 2.0 ± 0.5
skin | 3.20 ± 0.33 | 0.705 ± 0.013 | 0.46 ± 0.09

*SD = standard deviation

Microbiology:

The primary action of fluoroquinolones is to inhibit the bacterial enzyme, DNA gyrase. In susceptible organisms, fluoroquinolones are rapidly bactericidal at relatively low concentrations. Marbofloxacin is bactericidal against a broad range of gram-negative and gram-positive organisms. The minimum inhibitory concentrations (MICs) of pathogens isolated in clinical field studies performed in the United States were determined using National Committee for Clinical Laboratory Standards (NCCLS) standards, and are shown in Tables 4 and 5.

Table 4. MIC Values* (μg/mL) of marbofloxacin against pathogens isolated from skin, soft tissue and urinary tract infections in dogs enrolled in clinical studies conducted during 1994–1996.

Organism | No. of Isolates | MIC50 | MIC90 | MIC Range
Staphylococcus intermedius | 135 | 0.25 | 0.25 | 0.125-2
Escherichia coli | 61 | 0.03 | 0.06 | 0.015-2
Proteus mirabilis | 35 | 0.06 | 0.125 | 0.03-0.25
Beta-hemolytic Streptococcus, (not Group A or Group B) | 25 | 1 | 2 | 0.5-16
Streptococcus, Group D enterococcus | 16 | 1 | 4 | 0.008-4
Pasteurella multocida | 13 | 0.015 | 0.06 | ≤0.008-0.5
Staphylococcus aureus | 12 | 0.25 | 0.25 | 0.25-0.5
Enterococcus faecalis | 11 | 2 | 2 | 1-4
Klebsiella pneumoniae | 11 | 0.06 | 0.06 | 0.01-0.06
Pseudomonas spp. | 9 | ** | ** | 0.06-1
Pseudomonas aeruginosa | 7 | ** | ** | 0.25-1

* The correlation between in vitro susceptibility data (MIC) and clinical response has not been determined.
**MIC50 and MIC90 not calculated due to insufficient number of isolates.

Table 5: MIC Values* (μg/mL) of marbofloxacin against pathogens isolated from skin and soft tissue infections in cats enrolled in clinical studies conducted in 1995 and 1998.

Organism | No. of Isolates | MIC50 | MIC90 | MIC Range
Pasteurella multocida | 135 | 0.03 | 0.06 | ≤0.008-0.25
Beta-hemolytic Streptococcus | 22 | 1 | 1 | 0.06-1
Staphylococcus aureus | 21 | 0.25 | 0.5 | 0.125-1
Corynebacterium spp. | 14 | 0.5 | 1 | 0.25-2
Staphylococcus intermedius | 11 | 0.25 | 0.5 | 0.03-0.5
Enterococcus faecalis | 10 | 2.0 | 2.0 | 1.0-2.0
Escherichia coli | 10 | 0.03 | 0.03 | 0.015-0.03
Bacillus spp. | 10 | 0.25 | 0.25 | 0.125-0.25

*The correlation between in vitro susceptibility data (MIC) and clinical response has not been determined.

INDICATIONS AND USAGE:

Marbofloxacin Chewable Tablets are indicated for the treatment of infections in dogs and cats associated with bacteria susceptible to marbofloxacin.

CONTRAINDICATIONS:

Marbofloxacin and other quinolones have been shown to cause arthropathy in immature animals of most species tested, the dog being particularly sensitive to this side effect. Marbofloxacin is contraindicated in immature dogs during the rapid growth phase (small and medium breeds up to 8 months of age, large breeds up to 12 months of age and giant breeds up to 18 months of age). Marbofloxacin is contraindicated in cats under 12 months of age. Marbofloxacin is contraindicated in dogs and cats known to be hypersensitive to quinolones.

WARNING:

For use in animals only. Keep out of reach of children. Avoid contact with eyes. In case of contact, immediately flush eyes with copious amounts of water for 15 minutes. In case of dermal contact, wash skin with soap and water. Consult a physician if irritation persists following ocular or dermal exposure. Individuals with a history of hypersensitivity to fluoroquinolones should avoid this product. In humans, there is a risk of user photosensitization within a few hours after excessive exposure to quinolones. If excessive accidental exposure occurs, avoid direct sunlight.

Keep marbofloxacin in a secure location out of reach of dogs, cats, and other animals to prevent accidental ingestion or overdose.

PRECAUTIONS:

Quinolones should be used with caution in animals with known or suspected central nervous system (CNS) disorders. In such animals, quinolones have, in rare instances, been associated with CNS stimulation which may lead to convulsive seizures. Quinolones have been shown to produce erosions of cartilage of weight-bearing joints and other signs of arthropathy in immature animals of various species. The use of fluoroquinolones in cats has been reported to adversely affect the retina. Such products should be used with caution in cats. The safety of marbofloxacin in animals used for breeding purposes, pregnant, or lactating has not been demonstrated.

ADVERSE REACTIONS:

The following clinical signs were reported during the course of clinical field studies in dogs receiving marbofloxacin at dosages up to 2.5 mg/lb daily: decreased or loss of appetite (5.4%), decreased activity (4.4%), and vomiting (2.9%). The following signs were reported in less than 1% of cases in dogs: increased thirst, soft stool/diarrhea, behavioral changes, shivering/shaking/tremors, and ataxia. One dog which had a seizure the day before study enrollment experienced a seizure while on marbofloxacin therapy.

The following clinical signs were reported during clinical field studies in cats receiving 1.25 mg/lb/day: diarrhea (2.1%) and soft stool (1.4%). Vomiting was reported in less than 1% of cases in cats.

DOSAGE AND ADMINISTRATION:

The recommended dosage for oral administration to dogs and cats is 1.25 mg marbofloxacin per lb of body weight once daily, but the dosage may be safely increased to 2.5 mg/lb.

For the treatment of skin and soft tissue infections, Marbofloxacin Chewable Tablets should be given for 2–3 days beyond the cessation of clinical signs for a maximum of 30 days. For the treatment of urinary tract infections, Marbofloxacin Chewable Tablets should be administered for at least 10 days. If no improvement is noted within 5 days, the diagnosis should be re-evaluated and a different course of therapy considered.

Drug Interactions:

Compounds (e.g., sucralfate, antacids, and mineral supplements) containing divalent and trivalent cations (e.g., iron, aluminum, calcium, magnesium, and zinc) can interfere with the absorption of quinolones which may result in a decrease in product bioavailability. Therefore, the concomitant oral administration of quinolones with foods, supplements, or other preparations containing these compounds should be avoided.

EFFECTIVENESS CONFIRMATION:

Clinical effectiveness was confirmed in bacterial skin and soft tissue infections in dogs and cats and urinary tract infections (cystitis) in dogs associated with bacteria susceptible to marbofloxacin. Bacterial pathogens isolated in clinical field studies are provided in the Microbiology section.

TARGET ANIMAL SAFETY

Dogs:
The toxicity of marbofloxacin was assessed in 12- to 14-month-old beagle dogs administered marbofloxacin at 2.5, 7.5 and 12.5 mg/lb/day for 42 days. Vomiting, reddened skin (usually involving the ears) and reddened mucous membranes were occasionally observed in all groups, including controls, but were noted most frequently in the 12.5 mg/lb group. Decreased food consumption and weight loss were significant in the 7.5 mg/lb and 12.5 mg/lb groups. No clinical lameness was noted in any of the treated animals. Minimal to slight lesions in the articular cartilage were observed in 1/8 placebo-treated animals and in 3/8 animals given 12.5 mg marbofloxacin/lb. Macroscopically, these lesions were vesicles, raised areas, or depressed, light-colored areas. Microscopically, these lesions were characterized by the presence of one or more of the following: fissuring, erosion, chondrocyte proliferation, fibrillation, or vertical splitting of the articular cartilage. These cartilage lesions in treated dogs were similar to those in control dogs, and were not typical of those produced by fluoroquinolones. In addition to the above pathologic alterations, red areas of articular cartilage were noted macroscopically in 0/8 placebo-treated dogs and in 2/8 dogs from each of the three marbofloxacin-treated groups. These areas usually correlated microscopically with areas of vascularity of the articular surface, but could not be confirmed microscopically in all animals. They consisted of large blood vessels in mature fibrous connective tissue, with no indication of active vascularization due to drug-induced damage. They were considered most likely to be developmental anomalies or normal variations of the joint surface and were not considered to be related to drug treatment.

Marbofloxacin was administered to 12- to 14-month-old beagle dogs at a dosage of 25 mg/lb/day for 12 days. Decreased food consumption, vomiting, dehydration, excessive salivation, tremors, reddened skin, facial swelling, decreased activity and weight loss were seen in treated dogs. No clinical lameness was noted. As in the 42 day study, grossly visible, focal, red areas of articular cartilage were seen. These findings were noted in 2/6 placebo-treated dogs and in 4/6 marbofloxacin-treated dogs. The foci were areas of fibrocartilage with prominent vascularization or increased vascularization of subchondral bone. Due to the appearance microscopically and macroscopically, these red foci were described as likely to be developmental anomalies or normal variations in articular cartilage.

Marbofloxacin administered to 3- to 4-month-old, large breed, purpose-bred mongrel dogs at a dosage of 5 mg/lb/day for 14 days resulted in marked lameness in all dogs due to articular cartilage lesions. Lameness was accompanied by decreased appetite and activity.

Cats:
Marbofloxacin was administered for 42 consecutive days to 24 cats approximately 8 months old (8 cats per treatment group) at the dosages of 2.5, 7.5 and 12.5 mg/lb/day (5.5, 16.5 and 27.5 mg/kg/day). Treatment with marbofloxacin did not produce adverse effects on body weights, food consumption, serum chemistry, urinalysis or organ weight parameters. Decreased segmented neutrophil counts were observed in some cats in all treatment groups, including the placebo group, but mean counts were significantly lower in the marbofloxacin-treated groups. In some cats, absolute neutrophil counts were below normal reference values (as low as 615 neutrophils/μL in a marbofloxacin-treated cat and as low as 882 neutrophils/μL in a placebo-treated cat). Other hematological observations were not adversely affected. Clinical signs were occasionally noted in cats in the highest dosage group: excessive salivation in 4/8 cats and redness of ear pinnae in 2/8 cats. Macroscopic changes in the articular cartilage of femurs were seen in one cat receiving 7.5 mg/lb and in 3 cats receiving 12.5 mg/lb. Microscopically, these gross lesions were related to a focal or multifocal chondropathy. Microscopic chondropathy not associated with macroscopic observations was also present in one cat treated with 2.5 mg/lb daily (1X the upper end of the dose range) and one additional cat treated with 7.5 mg/lb daily. There was no evidence of lameness during the course of the study. A perivascular to diffuse dermatitis was seen microscopically in one mid-dose cat and 4 high-dose cats. Funduscopic exam by a board-certified ophthalmologist and histologic examination of retina and optic nerve by ocular pathologists revealed no lesions in any of the treatment groups.

Marbofloxacin was also administered orally to 6 cats approximately 8 months of age for 14 consecutive days at a dosage of 25 mg/lb/day (55 mg/kg/day). Clinical signs associated with drug intolerance were excessive salivation in 5/6 cats and redness of ear pinnae in all cats after 8 days of treatment. Emesis was noted occasionally in several cats and diminished activity was noted in one cat. Decreased food intake was noted in some animals, primarily males, when compared to controls. Perivascular to diffuse dermatitis was seen microscopically in the pinnae of all treated animals and in the standard skin samples of several animals. There was focal or multifocal articular chondropathy in 2/6 treated animals. One treated cat had a duodenal mucosal erosion and one treated cat had a pyloric ulcer. There were no observations of lameness and no adverse effects on hematology, clinical chemistry, urinalysis, or organ weight parameters. Funduscopic examination by a board-certified ophthalmologist and histologic examination of retina and optic nerve by ocular pathologists revealed no lesions.

A study was conducted to investigate the effect of marbofloxacin on articular cartilage of skeletally mature cats 12–14 months of age. Forty cats were randomly assigned to 4 groups of 10 cats each. Groups received placebo or marbofloxacin at dosages of 1.25, 3.75 or 7.5 mg/lb/day (2.75, 8.25 or 16.5 mg/kg/day) for 42 consecutive days. There were no treatment-related pathological changes in the joints or other tissues. Emesis and soft stools was noted in all treatment groups, including placebo, and increased in frequency with increasing dose and duration of treatment. Emesis was more apparent in the high-dose males.

STORAGE CONDITIONS:

Store at 20° to 25°C (68° to 77°F); excursions permitted between 15° and 30°C (59° and 86°F) [see USP Controlled Room Temperature].

HOW SUPPLIED:

Marbofloxacin Chewable Tablets are available in the following strengths of marbofloxacin and bottle sizes:
25 mg scored tablets supplied in bottles that contain 100 tablets (NDC No. 86101-016-11) or 250 tablets (NDC No. 86101-016-16)

50 mg scored tablets supplied in bottles that contain 100 tablets (NDC No. 86101-017-11) or 250 tablets (NDC No. 86101-017-16)

100 mg scored tablets supplied in a 50 tablet bottle (NDC No. 86101-018-50)
200 mg scored tablets supplied in a 50 tablet bottle (NDC No. 86101-019-50)

REFERENCES:

1. Schneider M, et al: Pharmacokinetics of marbofloxacin in dogs after oral and parenteral administration. J Vet Pharmacol Therap 19:56–61, 1996.

To report suspected adverse drug events, for technical assistance or to obtain a copy of the Safety Data Sheet, contact Felix Pharmaceuticals Private Limited at 1-833-571-1525. For additional information about adverse drug experience reporting for animal drugs, contact FDA at 1-888-FDA-VETS or http://www.fda.gov/reportanimalae

Approved by FDA under ANADA # 200-733

Distributed by:

Felixvet Inc.,
1300 NW Briarcliff Parkway,
Suite 100, Kansas City, Missouri 64150

Made in India

Neutral code no. MP/DRUGS/28/53/2020

Rev. December 2024

PRINCIPAL DISPLAY PANEL - 25 MG (100's count) BOTTLE LABEL

NDC: 86101-016-11

Marbofloxacin

Chewable Tablets

25 mg

For oral use in dogs and cats only

Antibacterial

Caution: Federal law restricts this drug to use by or on the order of a licensed veterinarian.

Federal law prohibits the extralabel use of this drug in food-producing animals.

Approved by FDA under ANADA # 200-733

100 Tablets

PRINCIPAL DISPLAY PANEL - 25 MG (250's count) BOTTLE LABEL

NDC: 86101-016-16

Marbofloxacin

Chewable Tablets

25 mg

For oral use in dogs and cats only

Antibacterial

Caution: Federal law restricts this drug to use by or on the order of a licensed veterinarian.

Federal law prohibits the extralabel use of this drug in food-producing animals.

Approved by FDA under ANADA # 200-733

250 Tablets

PRINCIPAL DISPLAY PANEL - 50 MG (100's count) BOTTLE LABEL

NDC: 86101-017-11

Marbofloxacin

Chewable Tablets

50 mg

For oral use in dogs only

Antibacterial

Caution: Federal law restricts this drug to use by or on the order of a licensed veterinarian.

Federal law prohibits the extralabel use of this drug in food-producing animals.

Approved by FDA under ANADA # 200-733

100 Tablets

PRINCIPAL DISPLAY PANEL - 50 MG (250's count) BOTTLE LABEL

NDC: 86101-017-16

Marbofloxacin

Chewable Tablets

50 mg

For oral use in dogs only

Antibacterial

Caution: Federal law restricts this drug to use by or on the order of a licensed veterinarian.

Federal law prohibits the extralabel use of this drug in food-producing animals.

Approved by FDA under ANADA # 200-733

250 Tablets

PRINCIPAL DISPLAY PANEL - 100 MG (50's count) BOTTLE LABEL

NDC: 86101-018-50

Marbofloxacin

Chewable Tablets

100 mg

For oral use in dogs only

Antibacterial

Caution: Federal law restricts this drug to use by or on the order of a licensed veterinarian.

Federal law prohibits the extra label use of this drug in food-producing animals.

Approved by FDA under ANADA # 200-733

50 Tablets

PRINCIPAL DISPLAY PANEL - 200 MG (50's count) BOTTLE LABEL

NDC: 86101-019-50

Marbofloxacin

Chewable Tablets

200 mg

For oral use in dogs only

Antibacterial

Caution: Federal law restricts this drug to use by or on the order of a licensed veterinarian.

Federal law prohibits the extralabel use of this drug in food-producing animals.

Approved by FDA under ANADA # 200-733

50 Tablets